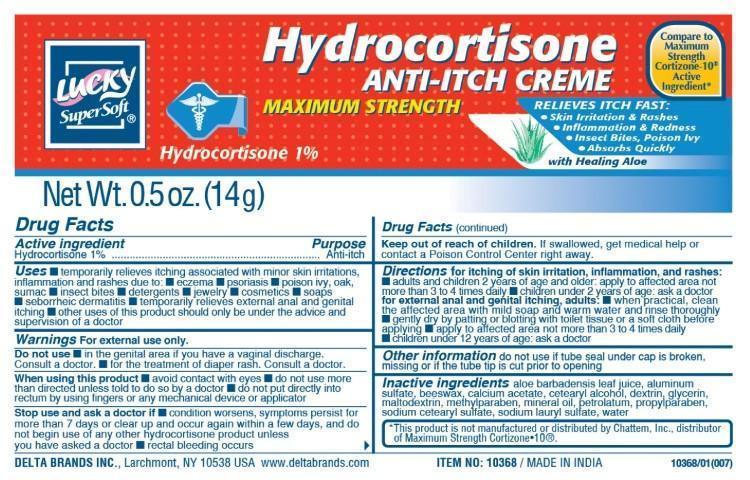 DRUG LABEL: Lucky SuperSoft
NDC: 47046-176 | Form: CREAM
Manufacturer: Anicare Pharmaceuticals Pvt. Ltd.
Category: otc | Type: HUMAN OTC DRUG LABEL
Date: 20201220

ACTIVE INGREDIENTS: HYDROCORTISONE 1 g/100 g
INACTIVE INGREDIENTS: ALOE VERA LEAF; ALUMINUM SULFATE; YELLOW WAX; CALCIUM ACETATE; CETOSTEARYL ALCOHOL; ICODEXTRIN; GLYCERIN; MALTODEXTRIN; METHYLPARABEN; MINERAL OIL; PETROLATUM; PROPYLPARABEN; SODIUM CETOSTEARYL SULFATE; SODIUM LAURYL SULFATE; WATER

Lucky HC Cream 1

Active Ingredient

Hydrocortisone 1%

Purpose

Anti-itch

Uses

■ temporarily relieves itching associated with minor skin irritations and rashes due to: ■ eczema ■ psoriasis ■ poison ivy, oak, sumac ■ insect bites ■ detergents ■ jewelry ■ cosmetics ■ soaps ■ seborrheic dermatitis ■ temporarily relieves external anal and genital itching ■ other uses of this product should be under the advice and supervision of a doctor

Warnings

For external use only

Do not use

■ in the genital area if you have vaginal discharge. Consult a doctor ■ for the treatment of diaper rash. Consult a doctor

When using this product

■ avoid contact with eyes ■ do not use more than directed unless told to do so by a doctor ■ do not put directly into the rectum by using fingers or any mechanical device or applicator

Stop use and ask a doctor if

■ the condition worsens, symptoms persist for more than 7 days or clear up and occur again wihin a few days, and do not begin use of any other hydrocortisone product unless you have asked a doctor ■ rectal bleed occurs

Keep out of reach of children

If swallowed, get medical help or contact a Poison Control Center right away

Directions

■ for itching of skin irritation, inflammation and rashes: ■ adults and children 2 years of age and older: apply to affected
area not more than 3 to 4 times daily ■ children under 2 years of age: ask a doctor

for external anal and genital itching, adults: ■ when practical, clean the affected area with mild soap and water and rinse thoroughly ■ gently dry by patting or blotting with toilet tissue or a soft cloth before applying ■ apply to affected area not more than 3 to 4 times daily ■ children under 12 years of age: ask a doctor

Other information

do not use if tube seal under cap is broken, missing or if the tube tip is cut prior to opening

Inactive ingredients

aloe barbadensis leaf juice, aluminum sulfate, beeswax, calcium acetate, cetearyl alcohol, dextrin, glycerin, maltodextrin, methylparaben, mineral oil, petrolatum, propylparaben, sodium cetearyl sulfate, sodium lauryl sulfate, water